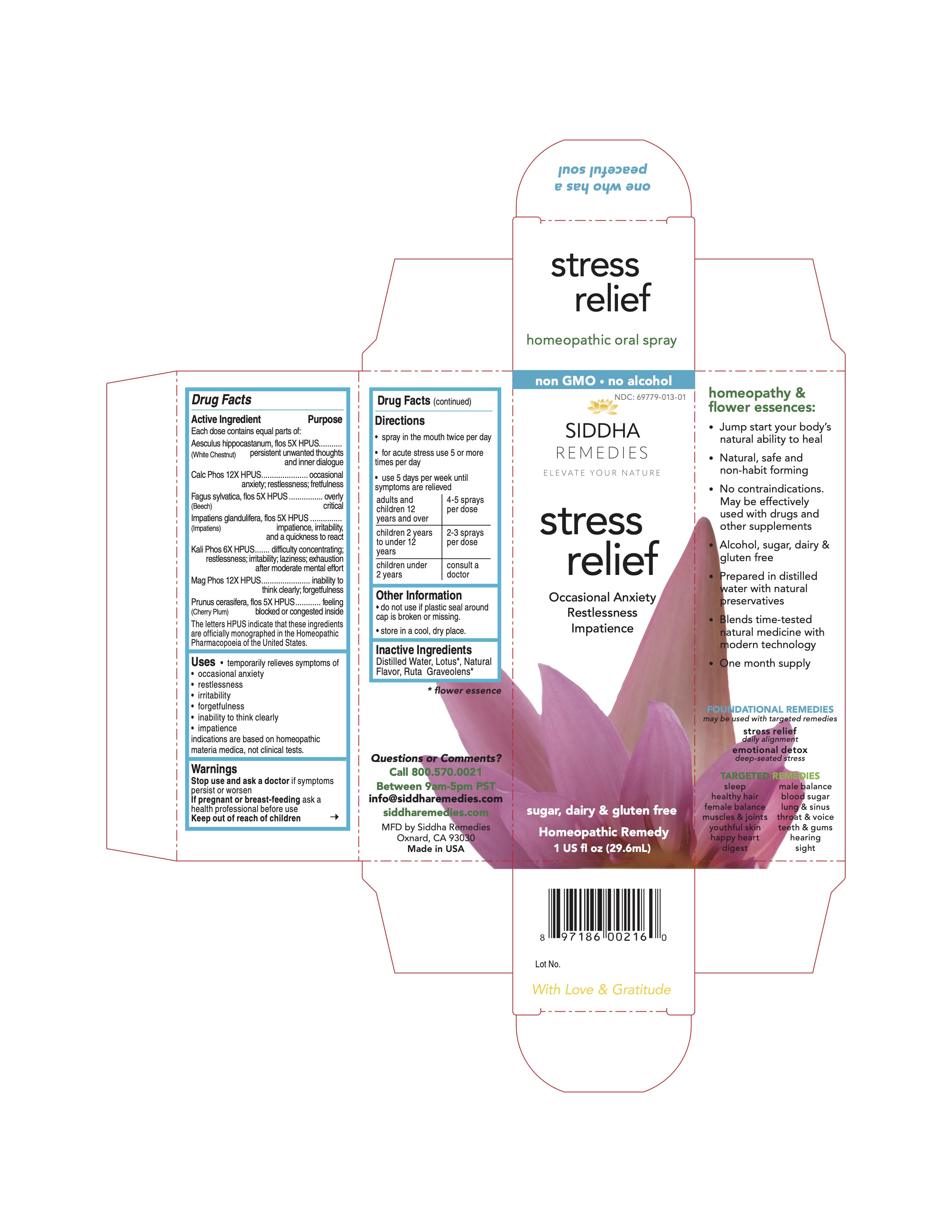 DRUG LABEL: stress relief
NDC: 69779-013 | Form: SPRAY
Manufacturer: Siddha Flower Essences LLC
Category: homeopathic | Type: HUMAN OTC DRUG LABEL
Date: 20251231

ACTIVE INGREDIENTS: AESCULUS HIPPOCASTANUM FLOWER 5 [hp_X]/29.6 mL; TRIBASIC CALCIUM PHOSPHATE 12 [hp_X]/29.6 mL; FAGUS SYLVATICA FLOWERING TOP 5 [hp_X]/29.6 mL; IMPATIENS GLANDULIFERA FLOWER 5 [hp_X]/29.6 mL; POTASSIUM PHOSPHATE, DIBASIC 6 [hp_X]/29.6 mL; MAGNESIUM PHOSPHATE, DIBASIC TRIHYDRATE 12 [hp_X]/29.6 mL; PRUNUS CERASIFERA FLOWER 5 [hp_X]/29.6 mL
INACTIVE INGREDIENTS: WATER; NELUMBO NUCIFERA FLOWER; RUTA GRAVEOLENS FLOWERING TOP

Drug Facts

Active Ingredient

Each dose contains equal parts of:

Aesculus hippocastanum, flos (White Chestnut) 5X HPUS
Calc Phos 12X HPUS
Fagus sylvatica, flos (Beech) 5X HPUS
Impatiens glandulifera, flos (Impatiens) 5X HPUS
Kali Phos 6X HPUS
Mag Phos 12X HPUS
Prunus cerasifera, flos (Cherry Plum) 5X HPUS

Purpose

Each dose contains equal parts of:
Aesculus hippocastanum, flos (White Chestnut) 5X HPUS......persistent unwanted thoughts and inner dialogue
Calc Phos 12X HPUS..........................................................occasional anxiety; restlessness; fretfulness
Fagus sylvatica, flos (Beech) 5X HPUS................................overly critical
Impatiens glandulifera, flos (Impatiens) 5X HPUS..................impatience, irritability, and quickness to react
Kali Phos 6X HPUS.............................................................difficulty concentrating; restlessness; irritability; laziness; exhaustion after moderate mental effort
Mag Phos 12X HPUS..........................................................inability to think clearly; forgetfulness
Prunus cerasifera, flos (Cherry Plum) 5X HPUS....................feeling blocked or congested inside
The letters HPUS indicate that these ingredients are officially monographed in the Homeopathic Pharmacopoeia of the United States.

Uses

- temporarily relives symptoms of:
- occasional anxiety
- restlessness
- irritability
- forgetfulness
- inability to think clearly
- impatience

indications are based on homeopathic materia medica, not clinical tests.

Warnings

Stop use and ask a doctor if symptoms persist or worsen

PREGNANCY OR BREAST FEEDING

If pregnant or breast-feeding ask a health professional before use

Keep out of reach of children

Directions

- spray in mouth twice per day
- for acute stress use 5 or more times per day
- use 5 days per week until symptoms are relieved

adults and children 12 years and over | 4-5 sprays per dose
children 2 years to under 12 years | 2-3 sprays per dose
children under 2 years | consult a doctor

Other Information

- do not use if plastic seal around cap is broken or missing.
- store in a cool, dry place.

Inactive Ingredients

Lotus*, Natural Flavor, Purified Water, Ruta Graveolens*

*flower essence

Questions or Comments?
Call 800.570.0021
Between 9am-5pm PST
info@siddhaflowers.com
siddhaflowers.com
MFD by Siddha Flower Essences
Oxnard, CA 93030
Made in USA

Side Panel

homeopathy and flower essences:

- Jump start your body's natural ability to heal
- Natural, safe and non-habit forming
- No contraindications. May be effectively used with drugs and other supplements
- Alcohol, sugar, dairy and gluten free
- Prepared in purified water with natural preservatives
- Blends time-tested natural medicine with modern technology
- One month supply

FOUNDATIONAL REMEDIES
may be used with targeted remedies
stress relief
daily alignment
emotional detox
deep-seated stress
TARGETED REMEDIES
sleep male balance
healthy hair blood sugar
female balance lung and sinus
muscles and joints throat and voice
youthful skin teeth and gums
happy heart hearing
digestion sight

Principal Display Panel

non GMO - no alcohol
siddha cell salts + flower essences
stress relief
Occasional Anxiety
Restlessness
Impatience
sugar, dairy and gluten free
Homeopathic Remedy
1 US fl oz (29.6mL)